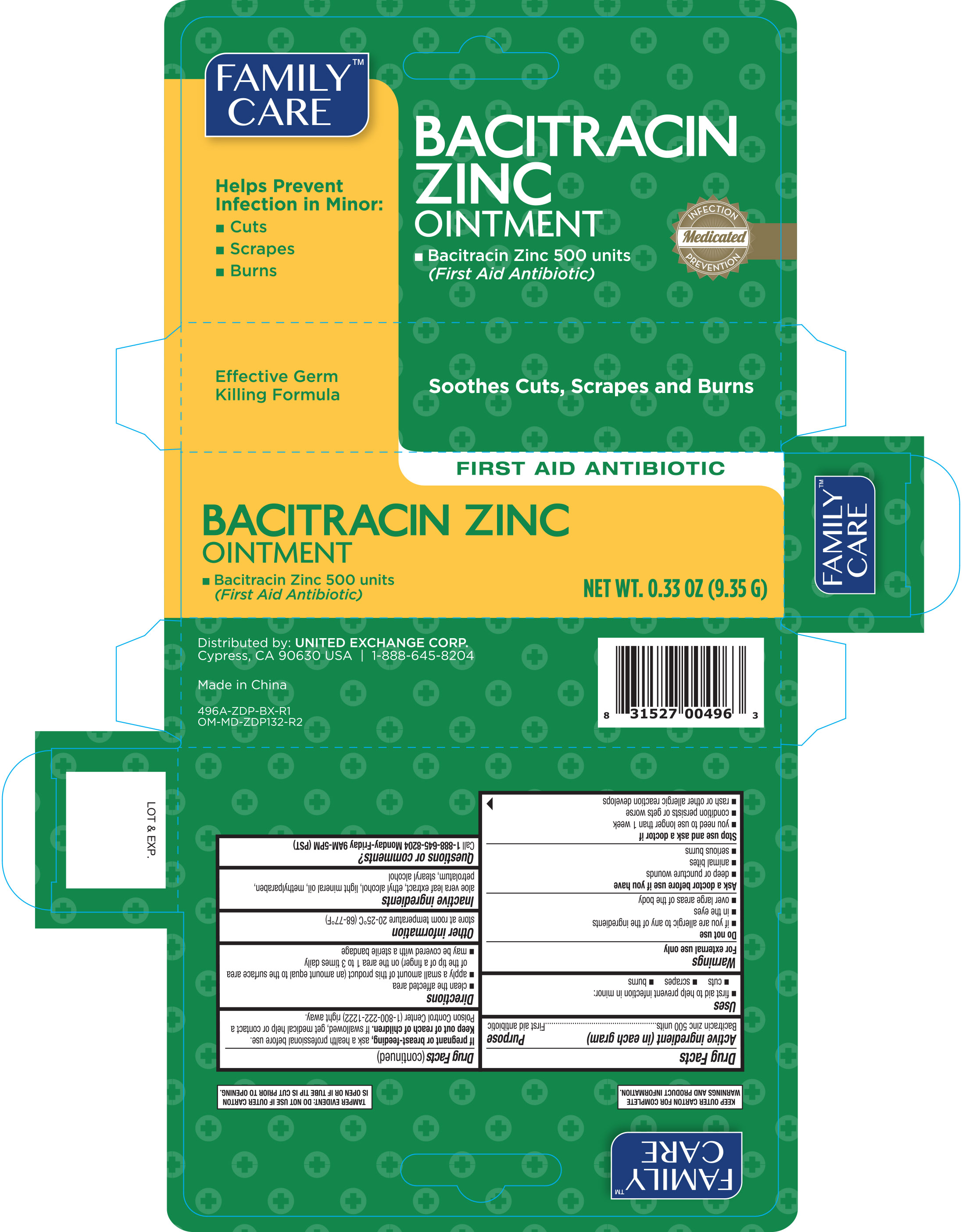 DRUG LABEL: Family Care First Aid
NDC: 65923-491 | Form: OINTMENT
Manufacturer: United Exchange Corp.
Category: otc | Type: HUMAN OTC DRUG LABEL
Date: 20251021

ACTIVE INGREDIENTS: BACITRACIN ZINC 500 [USP'U]/1 g
INACTIVE INGREDIENTS: METHYLPARABEN; STEARYL ALCOHOL; LIGHT MINERAL OIL; ALCOHOL; PETROLATUM; ALOE VERA LEAF

Family Care Bacitracin Zinc Ointment 0.33 oz 496A ZDP

Active ingredient (in each gram) Purpose

Bacitracin Zinc 500 units..............................................First aid antibiotic

Uses

- first aid to help prevent infection in minor:
- cuts
- scrapes
- burns

Warnings

For external use only

Do not use

- if you are allergic to any of the ingredients
- in the eyes
- over large areas of the body

Ask a doctor before use if you have

- deep or puncture wounds
- animal bites
- serious burns

Stop use and ask a doctor if

- you need to use longer than 1 week
- condition persists or gets worse
- rash or other allergic reaction develops

PREGNANCY OR BREAST FEEDING

If pregnant or breast-feeding, ask a health professional before use.

Keep out of reach of children. If swallowed, get medical help or contact a Poison Control Center (1-800-222-1222) right away.

Directions

- clean the affected area
- apply a small amount of this product (an amount to the surface area of the tip of a finger) on the area 1 to 3 times daily
- may be covered with a sterile bandage

Other information

store at room temperature 20-25°C (68-77°F)

Inactive ingredients

aloe vera leaf extract, ethyl alcohol, light mineral oil, methylparaben, petrolatum stearyl alcohol

DOSAGE AND ADMINISTRATION

Distributed by: United Exchange Corp.

Cypress, CA 90630 USA

Made in China